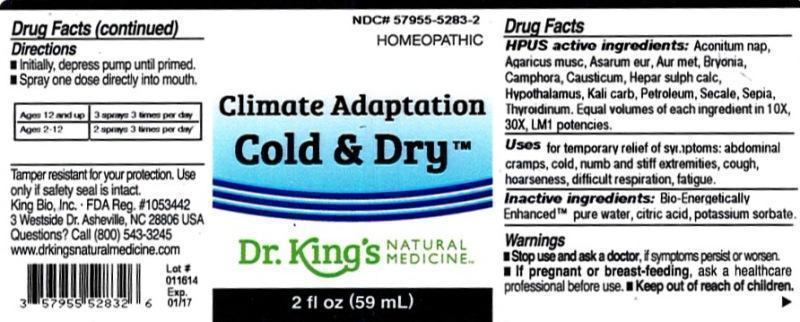 DRUG LABEL: Climate Adaptation Cold and Dry
NDC: 57955-5283 | Form: LIQUID
Manufacturer: King Bio Inc.
Category: homeopathic | Type: HUMAN OTC DRUG LABEL
Date: 20140204

ACTIVE INGREDIENTS: ACONITUM NAPELLUS 10 [hp_X]/59 mL; AMANITA MUSCARIA FRUITING BODY 10 [hp_X]/59 mL; ASARUM EUROPAEUM 10 [hp_X]/59 mL; GOLD 10 [hp_X]/59 mL; BRYONIA ALBA ROOT 10 [hp_X]/59 mL; CAMPHOR (NATURAL) 10 [hp_X]/59 mL; CAUSTICUM 10 [hp_X]/59 mL; CALCIUM SULFIDE 10 [hp_X]/59 mL; BOS TAURUS HYPOTHALAMUS 10 [hp_X]/59 mL; POTASSIUM CARBONATE 10 [hp_X]/59 mL; KEROSENE 10 [hp_X]/59 mL; CLAVICEPS PURPUREA SCLEROTIUM 10 [hp_X]/59 mL; SEPIA OFFICINALIS JUICE 10 [hp_X]/59 mL; THYROID, UNSPECIFIED 10 [hp_X]/59 mL
INACTIVE INGREDIENTS: WATER; CITRIC ACID MONOHYDRATE; POTASSIUM SORBATE

Climate Adaptation Cold and Dry™

ACTIVE INGREDIENT

Drug Facts__________________________________________________________________________________________________________

HPUS active ingredients: Aconitum napellus, Agaricus muscarius, Asarum europaeum, Aurum metallicum, Bryonia, Camphora, Causticum, Hepar sulphuris calcareum, Hypothalamus, Kali carbonicum, Petroleum, Secale cornutum, Sepia, Thyroidinum. Equal volumes of each ingredient in 10X, 30X, LM1 potencies.

INDICATIONS AND USAGE

Uses for temporary relief of symptoms: abdominal cramps, cold, numb and stiff extremities, cough, hoarseness, difficult respiration, fatigue.

Inactive Ingredients:

Bio-Energetically Enhanced™ pure water, citric acid and potassium sorbate.

Warnings

- Stop use and ask a doctor, if symptoms persist or worsen.

- If pregnant or breast-feeding, ask a healthcare professional before use.

- Keep out of reach of children

DOSAGE AND ADMINISTRATION

- Initially, depress pump until primed.
- Spray one dose directly into mouth.
- Ages 12 and up - 3 sprays 3 times per day.
- Ages 2-12 - 2 sprays 3 times per day.

OTHER SAFETY INFORMATION

Tamper resistant for your protection. Use only if safety seal is intact.

PURPOSE

Uses for temporary relief of symptoms:

- abdominal cramps
- cold, numb and stiff extremities
- cough
- hoarseness difficult respiration
- fatigue